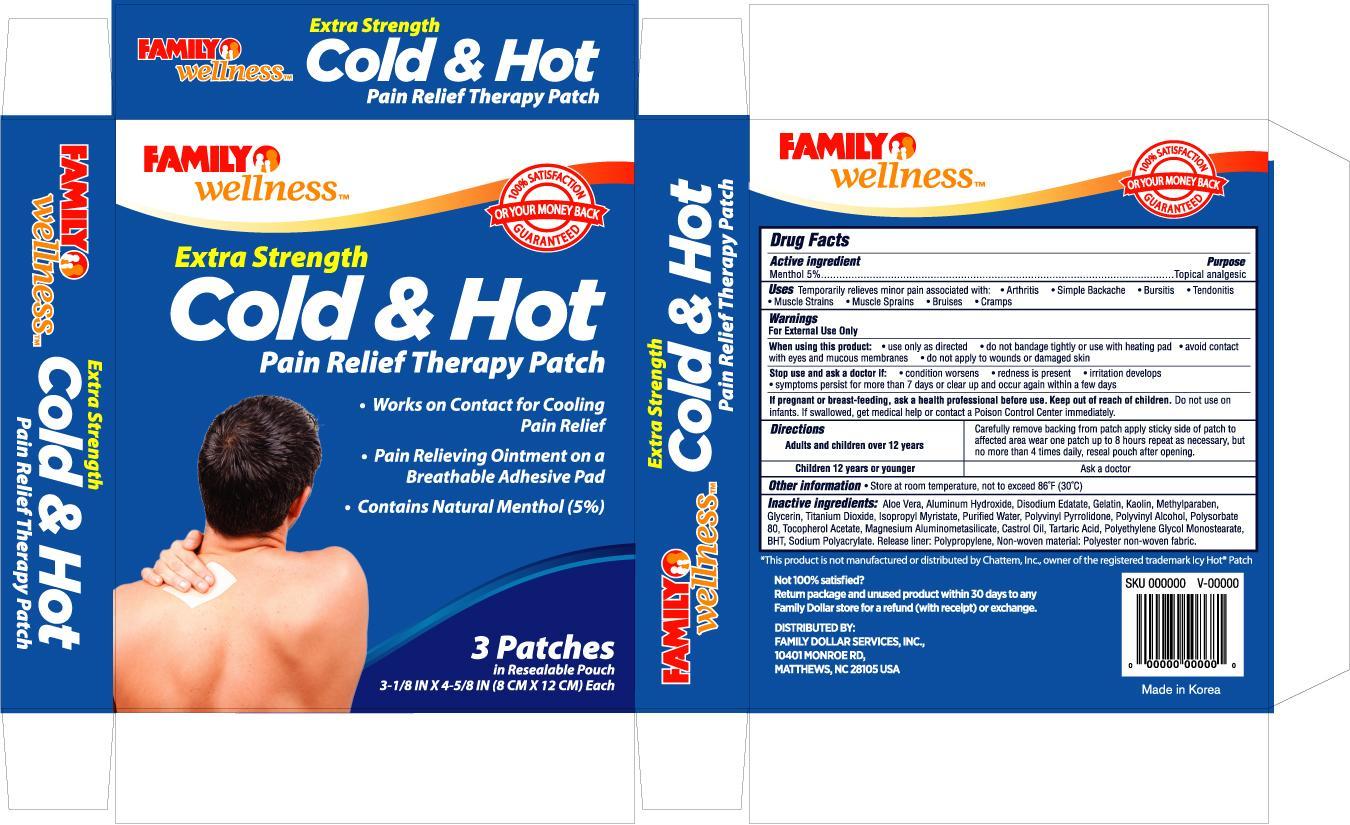 DRUG LABEL: FAMILY WELLNESS COLD AND HOT PAIN RELIEF
NDC: 55319-026 | Form: PATCH
Manufacturer: FAMILY DOLLAR
Category: otc | Type: HUMAN OTC DRUG LABEL
Date: 20121130

ACTIVE INGREDIENTS: MENTHOL 750 mg/1 1
INACTIVE INGREDIENTS: ALUMINUM HYDROXIDE; EDETATE DISODIUM; GELATIN; KAOLIN; METHYLPARABEN; GLYCERIN; TITANIUM DIOXIDE; ISOPROPYL MYRISTATE; WATER

Drug Facts

Active ingredient Purpose

Menthol 5% .....................................................................Topical analgesic

PURPOSE

Uses temporarily relieves minor pain associated with:

- arthritis
- simple backache
- bursitis
- tendonitis
- muscle strains
- muscle sprains
- bruises
- cramps

Warnings

For external use only

When using this product:

- use only as directed
- do not bandage tightly or use with heating pad
- avoid contact with eyes and mucous membranes
- do not apply to wounds or damaged skin

Stop use and ask a doctor if:

- condition worsens
- redness is present
- irritation develops
- symptoms persist for more than 7 days or clear up and occur again within a few days

PREGNANCY OR BREAST FEEDING

If pregnant or breast-feeding, ask a health professional before use.

Keep out of reach of children. Do not use on infants. If swallowed, get medical help or contact a Poison Control Center immediately

Directions

adults and children over 12 years:

- carefully remove backing from patch
- apply sticky side of patch to affected area

- repeat as necessary, but no more than 4 times daily

children 12 years of younger:

- ask a doctor

INACTIVE INGREDIENT

Inactive ingredients: Aloe Barbadensis Leaf Juice, Aluminum Hydroxide, Disodium EDTA, Gelatin, Kaolin, Methylparaben, Glycerin, Titanium Dioxide, Isopropyl Myristate, Purified Water,

Polyvinyl Pyrrolidone, Peg-4 Stearate, Polyvinyl Alcohol, Polysorbate 80, PVP, Tocopherol Acetate, Alumino Magnesium Metasilicate, Castor Oil, Tartaric Acid, BHT, Sodium Polyacrylate.

DOSAGE AND ADMINISTRATION

DISTRIBUTED BY:

FAMILY DOLLAR SERVICES, INC.

10401 MONROE RD.,

MATTHEWS, NC 28105 USA

MADE IN KOREA